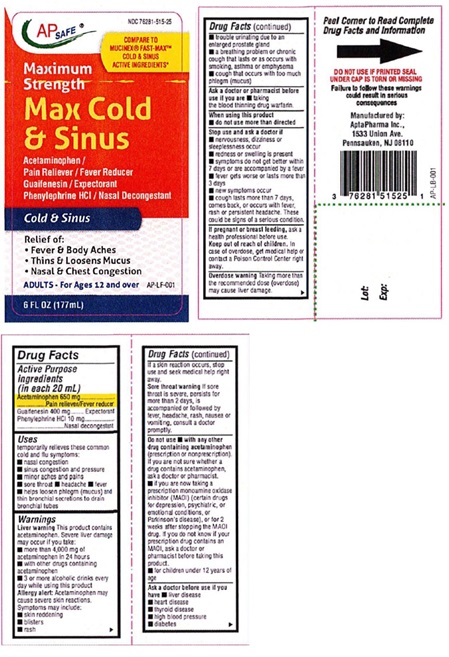 DRUG LABEL: Maximum strength Max Cold and Sinus
NDC: 76281-515 | Form: LIQUID
Manufacturer: AptaPharma Inc.
Category: otc | Type: HUMAN OTC DRUG LABEL
Date: 20240131

ACTIVE INGREDIENTS: ACETAMINOPHEN 650 mg/20 mL; GUAIFENESIN 400 mg/20 mL; PHENYLEPHRINE HYDROCHLORIDE 10 mg/20 mL
INACTIVE INGREDIENTS: ANHYDROUS CITRIC ACID; EDETATE DISODIUM; FD&C BLUE NO. 1; FD&C RED NO. 40; GLYCERIN; PROPYLENE GLYCOL; PROPYL GALLATE; WATER; SODIUM BENZOATE; SORBITOL; SUCRALOSE; XANTHAN GUM

Maximum strength Max Cold & Sinus

Drug Facts

Active ingredients
(in each 20 mL)
Acetaminophen 650 mg
Guaifenesin 400 mg
Phenylephrine HCl 10 mg

Purpose

Acetaminophen Pain reliever/Fever reducer
Guaifenesin Expectorant
Phenylephrine HCl Nasal decongestant

Uses

temporarily relieves these common cold and flu symptoms:
• nasal congestion
• sinus congestion and pressure
• minor aches and pains
• sore throat
• headache
• fever
• helps loosen phlegm (mucus) and thin bronchial secretions to drain bronchial tubes

Warnings

Liver warning
This product contains acetaminophen.
Severe liver damage may occur if you take:
• more than 4,000 mg of acetaminophen in 24 hours
• with other drugs containing acetaminophen
• 3 or more alcoholic drinks every day while using this product

Allergy alert: Acetaminophen may cause severe skin reactions. Symptoms may include:
• skin reddening
• blisters
• rash
If a skin reaction occurs, stop use and seek medical help right away.

Sore throat warning
If sore throat is severe, persists for more than 2 days, is accompanied or followed by fever, headache, rash, nausea or
vomiting, consult a doctor promptly.

Do not use.
• with any other drug containing acetaminophen (prescription or nonprescription). If you are not sure whether a drug
contains acetaminophen, ask a doctor or pharmacist.
• if you are now taking a prescription monoamine oxidase inhibitor (MAOI) (certain drugs for depression, psychiatric, or
emotional conditions, or Parkinson's disease), or for 2 weeks after stopping the MAOI drug. If you do not know if your
prescription drug contains an MAOI, ask a doctor or pharmacist before taking this product.
• for children under 12 years of age

Ask a doctor before use if you have
• liver disease
• heart disease
• thyroid disease
• high blood pressure
• diabetes
• trouble urinating due to an enlarged prostate gland
• a breathing problem or chronic cough that lasts or as occurs with smoking, asthma or emphysema
• cough that occurs with too much phlegm (mucus)

Ask a doctor or pharmacist before use if you are
• taking the blood thinning drug warfarin.

When using this product • do not use more than directed

Stop use and ask a doctor if
• nervousness, dizziness or sleeplessness occur
• redness or swelling is present
• symptoms do not get better within 7 days or are accompanied by a fever
• fever gets worse or lasts more than 3 days
• new symptoms occur
• cough lasts more than 7 days, comes back, or occurs with fever, rash or persistent headache. These could be signs of a
serious condition.

PREGNANCY OR BREAST FEEDING

If pregnant or breast feeding, ask a health professional before use.

Keep out of reach of children. In case of overdose, get
medical help or contact a Poison Control Center right
away.

OVERDOSAGE

Overdose warning
Taking more than the recommended dose (overdose) may cause liver damage. In case of overdose, get medical help or
contact a Poison Control Center right away. Quick medical attention is critical for adults as well as for children even if
you do not notice any signs or symptoms.

Directions
• take only as recommended (see Overdose warning)
• use dosage cup
• mL =milliliter
• do not take more than 6 doses in any 24-hour period

Age Dose
Adults & children 12 years and older | 20 mL every 4 hours
Children under 12 years of age | Do not use

Other information
• each 20 mL contains: sodium 10 mg
• dosage cup provided
• store between IS-30°C (59-86°F)
• do not refrigerate

Inactive ingredients
anhydrous citric acid, edetate disodium, FD&C Blue #1, FD&C Red #40, flavors, glycerin, propylene glycol, propyl gallate,
purified water, sodium benzoate, sorbitol, sucralose, Xanthan gum

QUESTIONS

Questions? Call weekdays from 9:30AM to 4:30 PM EST 1-877-798-5944

Maximum Strength MAX COLD & SINUS

AP SAFE NDC 76281-515-25

Compare to Mucinex® FAST-MAX™ Cold & Sinus
Active ingredients*
Maximum Strength
MAX COLD & SINUS

Acetaminophen /
Pain reliever/Fever Reducer
Guaifenesin /Expectorant
Phenylephrine HCl / Nasal decongestant
Cold & Sinus

Relief of:
• Fever & Bodyaches
• Thins & Loosens Mucus
• Nasal & Chest Congestion

Adults- For Ages 12 and over
6 FL OZ (177 mL)

DO NOT USE IF PRINTED SEAL UNDER CAP IS TORN OR MISSING
Failure to follow these warnings could result in serious consequences.

Manufactured by:
AptaPharma Inc.,
1533 Union Ave.
Pennsauken, NJ 08110

* This product is not manufactured or distributed by Reckitt Benckiser Inc., distributor of Mucinex® FAST-MAX™ Cold &
Sinus.

res